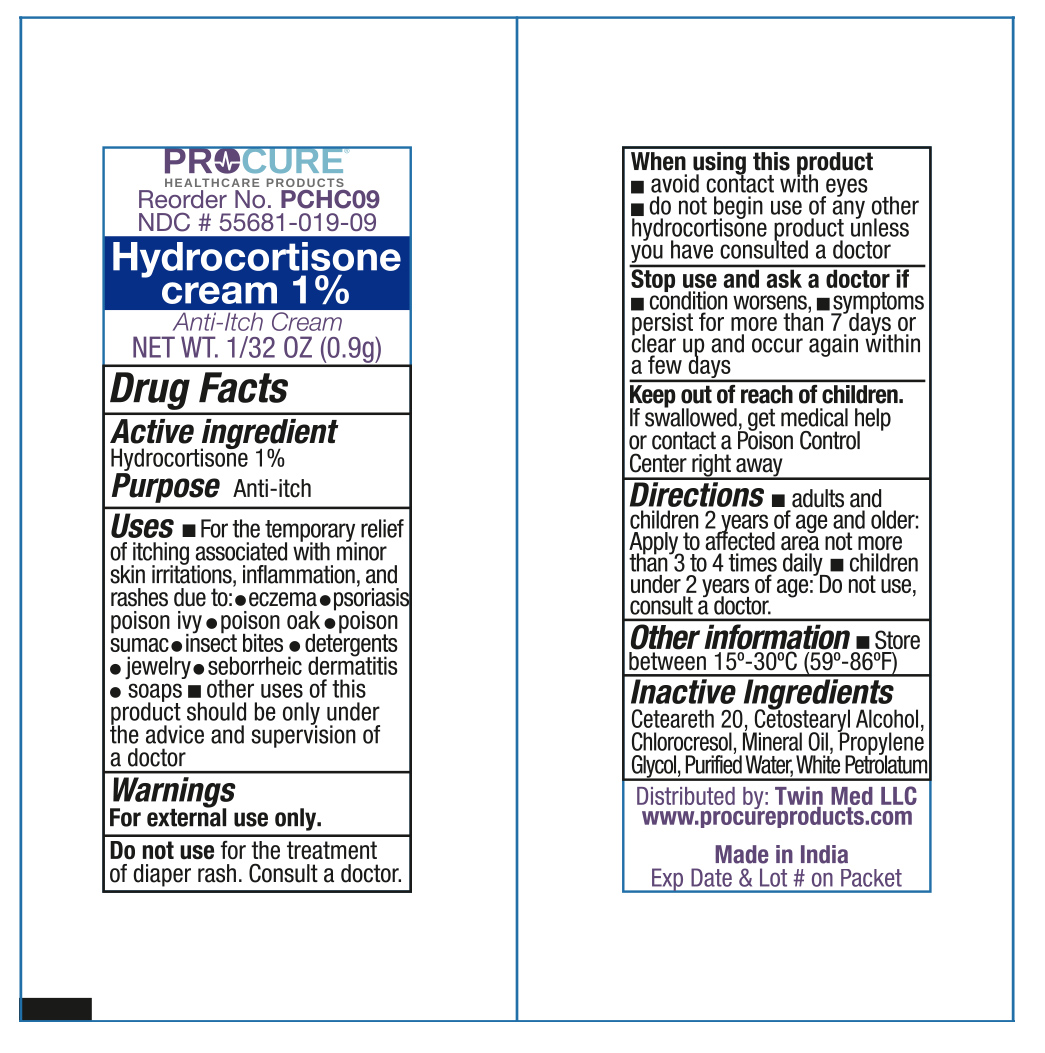 DRUG LABEL: ProCure Hydrocortisone 1%
NDC: 55681-019 | Form: CREAM
Manufacturer: Twin Med LLC
Category: otc | Type: HUMAN OTC DRUG LABEL
Date: 20250617

ACTIVE INGREDIENTS: HYDROCORTISONE 1 g/100 g
INACTIVE INGREDIENTS: CETOSTEARYL ALCOHOL; PROPYLENE GLYCOL; WATER; WHITE PETROLATUM; CHLOROCRESOL; MINERAL OIL; CETEARETH-20

Active Ingredient

Hydrocortisone 1%

PURPOSE

Anti-Itch

Uses

- For the temporary relief of itchng associtated with minor skin irritations, inflammation, and rashes due to eczema, psoriasis, poison ivy, poison oak, poison sumac, insect bites, detergents, jewelry, seborrheic dermatitis, and soaps
- Other uses of this product should be onl under the advise and supervision of a doctor

Warnings

for external use only.

Do not use for the treatment of diaper rash. Consult a doctor

Stop use and ask a doctor if

- condition worsens
- symptoms persist for more than 7 days or clear up and occur again within a few days

When using this product

- avoid contact with eyes
- do not begin use of any other hydrocortisone product unless you have consulted a doctor

Keep out of reach of children. If swallowed, get medical help or contact a Poison Control Center right away.

Directions

- Adults and children 2 years of age and older: apply to affected area not more than 3 to 4 times daily.
- Children under 2 years of age: do not use, consult a doctor

Inactive Ingredients

Ceteareth 20, Cetostearyl Alcohol, Chlorocresol, Mineral Oil, Propylene Glycol, Purified Water, White Petrolatum